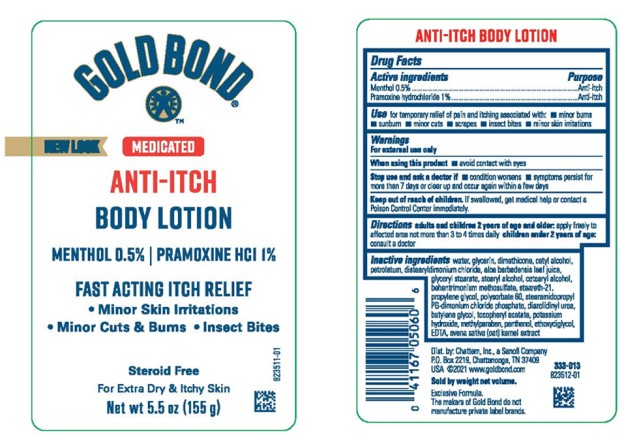 DRUG LABEL: Gold Bond Intensive Relief Anti-Itch
NDC: 41167-0507 | Form: LOTION
Manufacturer: Chattem, Inc.
Category: otc | Type: HUMAN OTC DRUG LABEL
Date: 20260114

ACTIVE INGREDIENTS: PRAMOXINE HYDROCHLORIDE 1 g/100 g; MENTHOL 0.5 g/100 g
INACTIVE INGREDIENTS: WATER; GLYCERIN; DIMETHICONE; CETYL ALCOHOL; PETROLATUM; DISTEARYLDIMONIUM CHLORIDE; ALOE VERA LEAF; GLYCERYL MONOSTEARATE; STEARYL ALCOHOL; CETOSTEARYL ALCOHOL; BEHENTRIMONIUM METHOSULFATE; STEARETH-21; PROPYLENE GLYCOL; POLYSORBATE 60; STEARAMIDOPROPYL PG-DIMONIUM CHLORIDE PHOSPHATE; DIAZOLIDINYL UREA; BUTYLENE GLYCOL; .ALPHA.-TOCOPHEROL ACETATE; POTASSIUM HYDROXIDE; METHYLPARABEN; PANTHENOL; DIETHYLENE GLYCOL MONOETHYL ETHER; EDETIC ACID; OAT

Gold Bond Intensive Relief Anti-Itch

GOLD BOND® Medicated

Intensive Relief Anti-Itch Lotion

Drug Facts

Active ingredients

Menthol 0.5%
Pramoxine hydrochloride 1%

Purpose

Anti-itch
Anti-itch

Use

for temporary relief of pain and itching associated with:

■ minor burns ■ sunburn ■ minor cuts ■ scrapes ■ insect bites ■ minor skin irritations

Warnings

For external use only

When using this product

■ avoid contact with eyes

Stop use and ask a doctor if

■ condition worsens

■ symptoms persist for more than 7 days or clear up and occur again within a few days

Keep out of reach of children.

If swallowed, get medical help or contact a Poison Control Center immediately.

Directions

adults and children 2 years of age and older: apply freely to affected area not more than 3 to 4 times daily

children under 2 years of age: consult a doctor

Inactive ingredients

water, glycerin, dimethicone, cetyl alcohol, petrolatum, distearyldimonium chloride, aloe barbadensis leaf juice, glyceryl stearate, stearyl alcohol, cetearyl alcohol, behentrimonium methosulfate, steareth-21, propylene glycol, polysorbate 60, stearamidopropyl PG-dimonium chloride phosphate, diazolidinyl urea, butylene glycol, tocopheryl acetate, potassium hydroxide, methylparaben, panthenol, ethoxydiglycol, EDTA, avena sativa (oat) kernel extract

PRINCIPAL DISPLAY PANEL

GOLD BOND
ANTI-ITCH LOTION
INTENSIVE RELIEF
Net wt 5.5 oz (155 g)